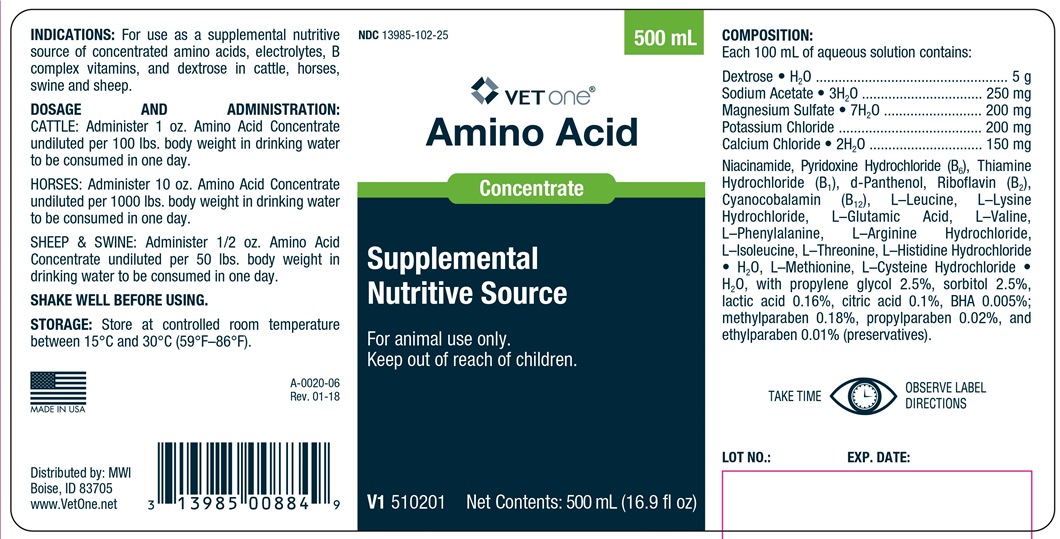 DRUG LABEL: AMINO ACID
NDC: 13985-102 | Form: CONCENTRATE
Manufacturer: MWI Veterinary Supply Co.
Category: animal | Type: OTC ANIMAL DRUG LABEL
Date: 20180423

ACTIVE INGREDIENTS: CALCIUM CHLORIDE ANHYDROUS 150 mg/100 mL; DEXTROSE MONOHYDRATE 5 g/100 mL; MAGNESIUM SULFATE HEPTAHYDRATE 200 mg/100 mL; POTASSIUM CHLORIDE 200 mg/100 mL; SODIUM ACETATE ANHYDROUS 250 mg/100 mL

Amino Acid Concentrate

INDICATIONS AND USAGE

SUPPLEMENTAL NUTRITIVE SOURCE

For Animal Use Only

Keep out of reach of children

INDICATIONS

For use as a supplemental nutritive source of concentrated amino acids, electrolytes, B complex vitamins, and dextrose in cattle, horses, swine and sheep.

DOSAGE AND ADMINISTRATION

CATTLE: Administer 1 oz. Amino Acid Concentrate per 100 lbs. body weight in drinking water to be consumed in one day.

HORSE: Administer 10 oz. Amino Acid Concentrate per 1000 lbs. body weight in drinking water to be consumed in one day.

SHEEP and SWINE: Administer 1/2 oz. Amino Acid Concentrate per 50 lbs. body weight in drinking water to be consumed in one day.

STORAGE

SHAKE WELL BEFORE USING.

Store at controlled room temperature between 15° and 30° C (59°-86°F)

TAKE TIME OBSERVE LABEL DIRECTIONS.

CONTENTS

Each 100 mL of aqueous solution contains:

Dextrose • H2O .......................... 5 g
Sodium Acetate • 3H2O ........ 250 mg
Magnesium Sulfate • 7H2O ... 200 mg
Potassium Chloride .............. 200 mg
Calcium Chloride • 2H2O .......150 mg

Comprised of : Niacinamide, Pyridoxine Hydrochloride (B6), Thiamine Hydrochloride (B1), d-Panthenol, Riboflavin (B2), Cyanocobalamin (B12), L-Leucine, L-Lysine Hydrochloride, L-Glutamic Acid, L-Valine, L-Phenylalanine, L-Arginine Hydrochloride, L-Isoleucine, L-Threonine, L-Histidine Hydrochloride • H2O, L-Methionine, L-Cysteine Hydrochloride • H2O, with propylene glycol 2.5%, sorbitol 2.5%, lactic acid 0.16%, citric acid 0.1%, BHA 0.005%, methylparaben 0.18%, propylparaben 0.02%, and ethylparaben 0.01% (preservatives).